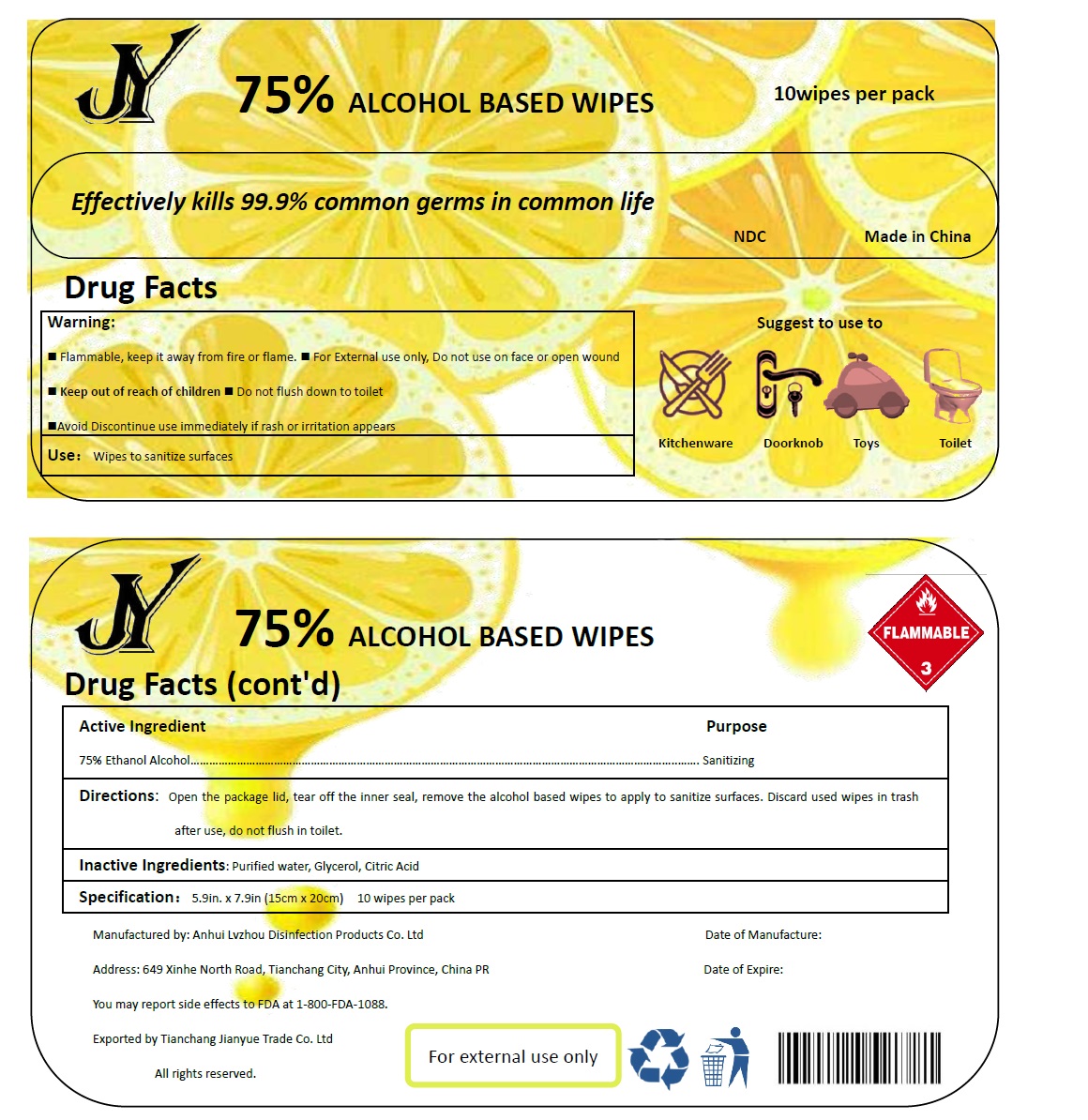 DRUG LABEL: alcohol wipes
NDC: 52985-900 | Form: CLOTH
Manufacturer: Anhui Oasis Disinfection Products Co., Ltd
Category: otc | Type: HUMAN OTC DRUG LABEL
Date: 20220114

ACTIVE INGREDIENTS: ALCOHOL 75 mL/100 mL
INACTIVE INGREDIENTS: CITRIC ACID MONOHYDRATE; WATER; GLYCERIN

52985-900 alcohol wipes 75% Ethyl Alcohol

Active Ingredient

Ethyl Alcohol 75%

Purpose

Sanitizing

Use

Wipes to sanitize surfaces.

WARNINGS

Flammable, keep it away from fire or flame. . For External use only, DO not use on face or open wound

1 Keep out of reach of children■Do not flush down to toilet
Avoid Discontinue use immediately if rash or irritation appears

■Keep out of reach of children.

Directions

Open the package lid, tear off the inner seal, remove the alcohol based wipes to apply to sanitize surfaces. Discard used wipes in trash after use, do not flush in toilet.

Inactive ingredients

Purified water, Glycerol, Citric Acid